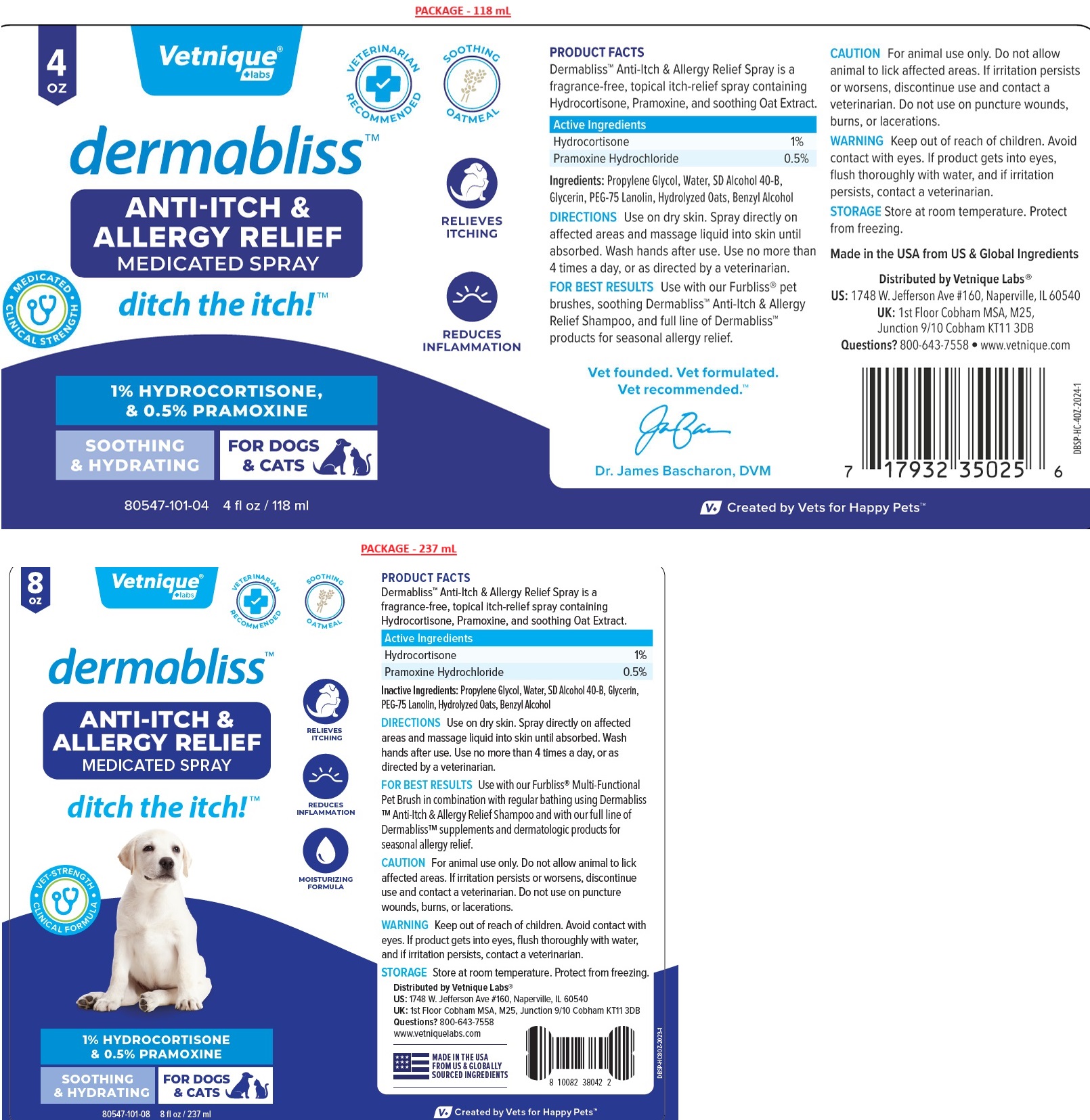 DRUG LABEL: Dermabliss ANTI-ITCH and ALLERGY RELIEF
NDC: 80547-101 | Form: SPRAY
Manufacturer: Vetnique Labs Llc
Category: animal | Type: OTC ANIMAL DRUG LABEL
Date: 20241024

ACTIVE INGREDIENTS: HYDROCORTISONE 10 mg/1 mL; PRAMOXINE HYDROCHLORIDE 5 mg/1 mL
INACTIVE INGREDIENTS: PROPYLENE GLYCOL; WATER; ALCOHOL; GLYCERIN; PEG-75 LANOLIN; OAT; BENZYL ALCOHOL

dermabliss™ ANTI-ITCH & ALLERGY RELIEF MEDICATED SPRAY

PRODUCT FACTS

Dermabliss™ Anti-Itch & Allergy Relief Spray is a fragrance-free, topical itch-relief spray containing Hydrocortisone, Pramoxine, and soothing Oat Extract.

Active Ingredients

Hydrocortisone 1%

Pramoxine Hydrochloride 0.5%

Ingredients:

Propylene Glycol, Water, SD Alcohol 40-B, Glycerin, PEG-75 Lanolin, Hydrolyzed Oats, Benzyl Alcohol

DIRECTIONS

Use on dry skin. Spray directly on affected areas and massage liquid into skin until absorbed. Wash hands after use. Use no more than 4 times a day, or as directed by a veterinarian.

FOR BEST RESULTS Use with our Furbliss® pet brushes, soothing Dermabliss™ Anti-Itch & Allergy Relief Shampoo, and full line of Dermabliss™ products for seasonal allergy relief.

CAUTION

For animal use only. Do not allow animal to lick affected areas. If irritation persists or worsens, discontinue use and contact a veterinarian. Do not use on puncture wounds, burns, or lacerations.

WARNING

Keep out of reach of children. Avoid contact with eyes. If product gets into eyes, flush thoroughly with water, and if irritation persists, contact a veterinarian.

STORAGE

Store at room temperature. Protect from freezing.

VETERINARIAN RECOMMENDED

SOOTHING OATMEAL

• MEDICATED • CLINICAL STRENGTH

ditch the itch!™

RELIEVES ITCHING

REDUCES INFLAMMATION

MOISTURIZING FORMULA

SOOTHING & HYDRATING

FOR DOGS & CATS

Vet founded. Vet formulated.
Vet recommended.™

Made in the USA from US & Global Ingredients

Distributed by Vetnique Labs®

US: 1748 W. Jefferson Ave #160, Naperville, IL 60540

UK: 1st Floor Cobham MSA, M25, Junction 9/10 Cobham KT11 3DB

Questions? 800-643-7558 • www.vetnique.com

V+ Created by Vets for Happy Pets™